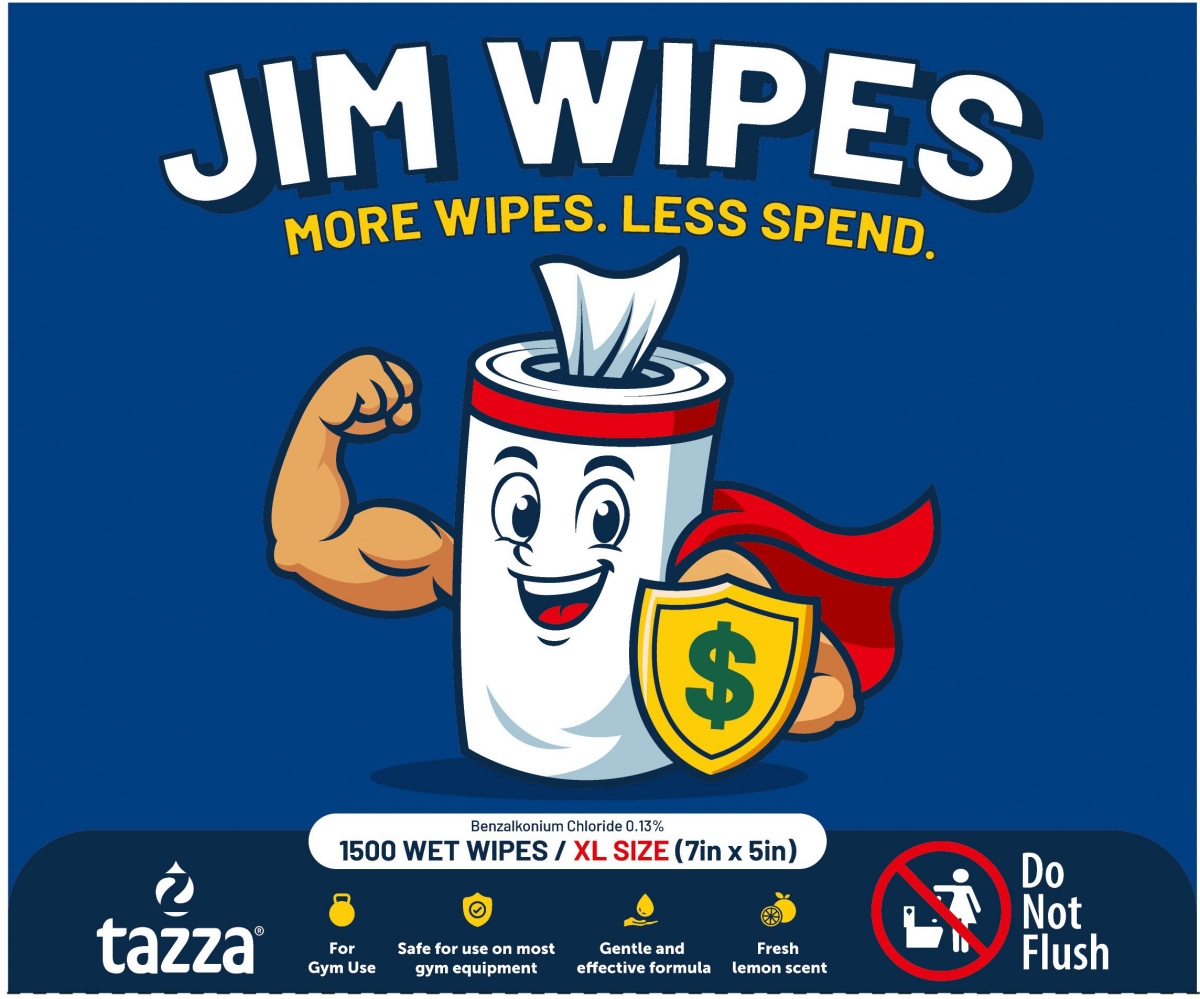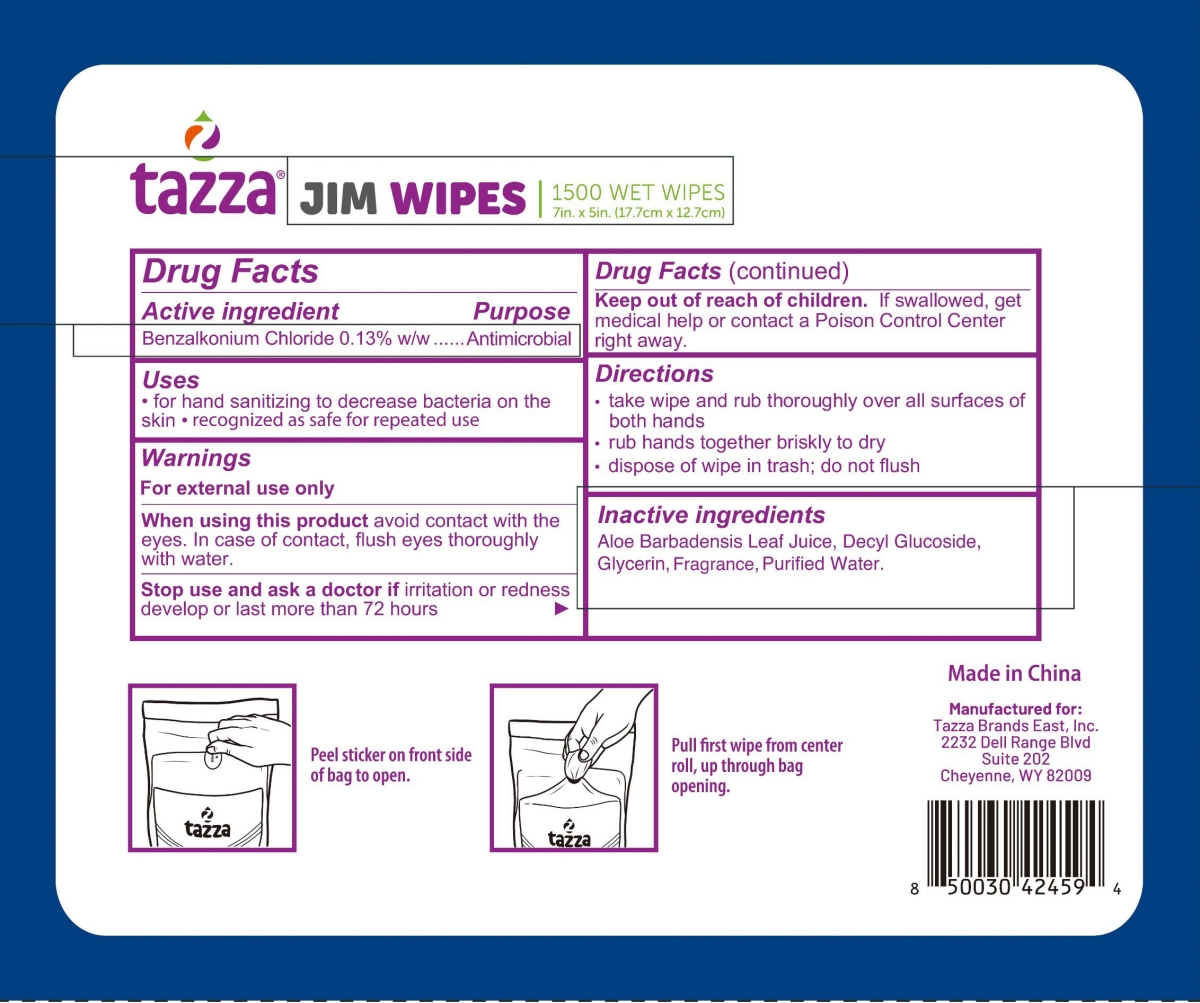 DRUG LABEL: tazza JIM WIPES
NDC: 76370-0039 | Form: CLOTH
Manufacturer: Tazza Brands East, Inc.
Category: otc | Type: HUMAN OTC DRUG LABEL
Date: 20251229

ACTIVE INGREDIENTS: BENZALKONIUM CHLORIDE 0.13 g/100 g
INACTIVE INGREDIENTS: DECYL GLUCOSIDE; ALOE VERA LEAF; GLYCERIN; WATER

76370-0039 tazza JIM WIPES

Active ingredient

Benzalkonium Chloride 0.13% w/w

Purpose

Antimicrobial

Uses

· for hand sanitizing to decrease bacteria on the skin · recognized as safe for repeated use

Warnings

For external use only

When using this product avoid contact with the eyes. In case of contact, flush eyes thoroughly with water.

Stop use and ask a doctor if irritation or redness develop or last more than 72 hours

Keep out of reach of children. If swallowed, get medical help or contact a Poison Control Center right away.

Directions

· take wipe and rub thoroughly over all surfaces of both hands

· rub hands together briskly to dry

· dispose of wipe in trash; do not flush

Inactive ingredients

Aloe Barbadensis Leaf Juice, Decyl Glucoside,

Glycerin, Fragrance, Purified Water.

PACKAGE LABEL

JIM WIPES
1500 WET WIPES / XL SIZE (7in × 5in)
NDC: 76370-0039-1